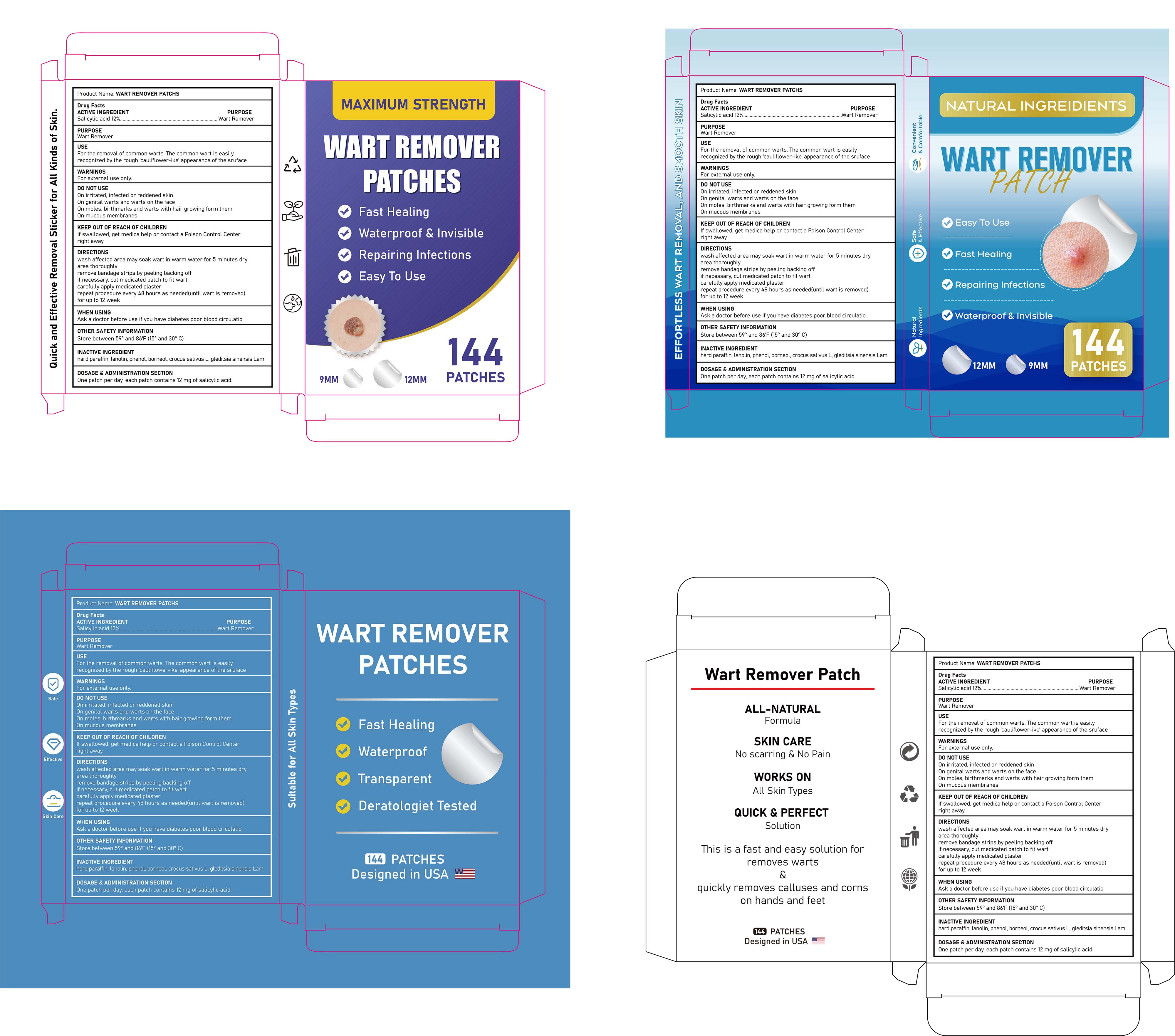 DRUG LABEL: WART REMOVER PATCHES
NDC: 85839-009 | Form: PATCH
Manufacturer: Shenzhen Finona Information Technology Co., Ltd
Category: otc | Type: HUMAN OTC DRUG LABEL
Date: 20250901

ACTIVE INGREDIENTS: SALICYLIC ACID 0.12 g/1 1
INACTIVE INGREDIENTS: GLEDITSIA SINENSIS WHOLE; BORNEOL; PHENOL; LANOLIN; CROCUS SATIVUS WHOLE; PARAFFIN

85839-009 WART REMOVER PATCHES

ACTIVE INGREDIENT

Salicylic acid 12%

PURPOSE

Wart Remover

INDICATIONS AND USAGE

For the removal of common warts. The common wart is easily recognized by the rough 'cauliflower-ike' appearance of the sruface

WARNINGS

For external use only.

DO NOT USE

On irritated, infected or reddened skin
On genital warts and warts on the face
On moles, birthmarks and warts with hair growing form them
On mucous membranes

Ask a doctor before use if you have diabetes poor blood circulatio

KEEP OUT OF REACH OF CHILDREN

If swallowed, get medica help or contact a Poison Control Center right away

DOSAGE AND ADMINISTRATION

wash affected area may soak wart in warm water for 5 minutes dryarea thoroughlyremove bandage strips by peeling backing offif necessary, cut medicated patch to fit wartcarefully apply medicated plasterrepeat procedure every 48 hours as needed(until wart is removed)for up to 12 week

INACTIVE INGREDIENT

hard paraffin
lanolin
phenol
borneol
crocus sativus L
gleditsia sinensis Lam